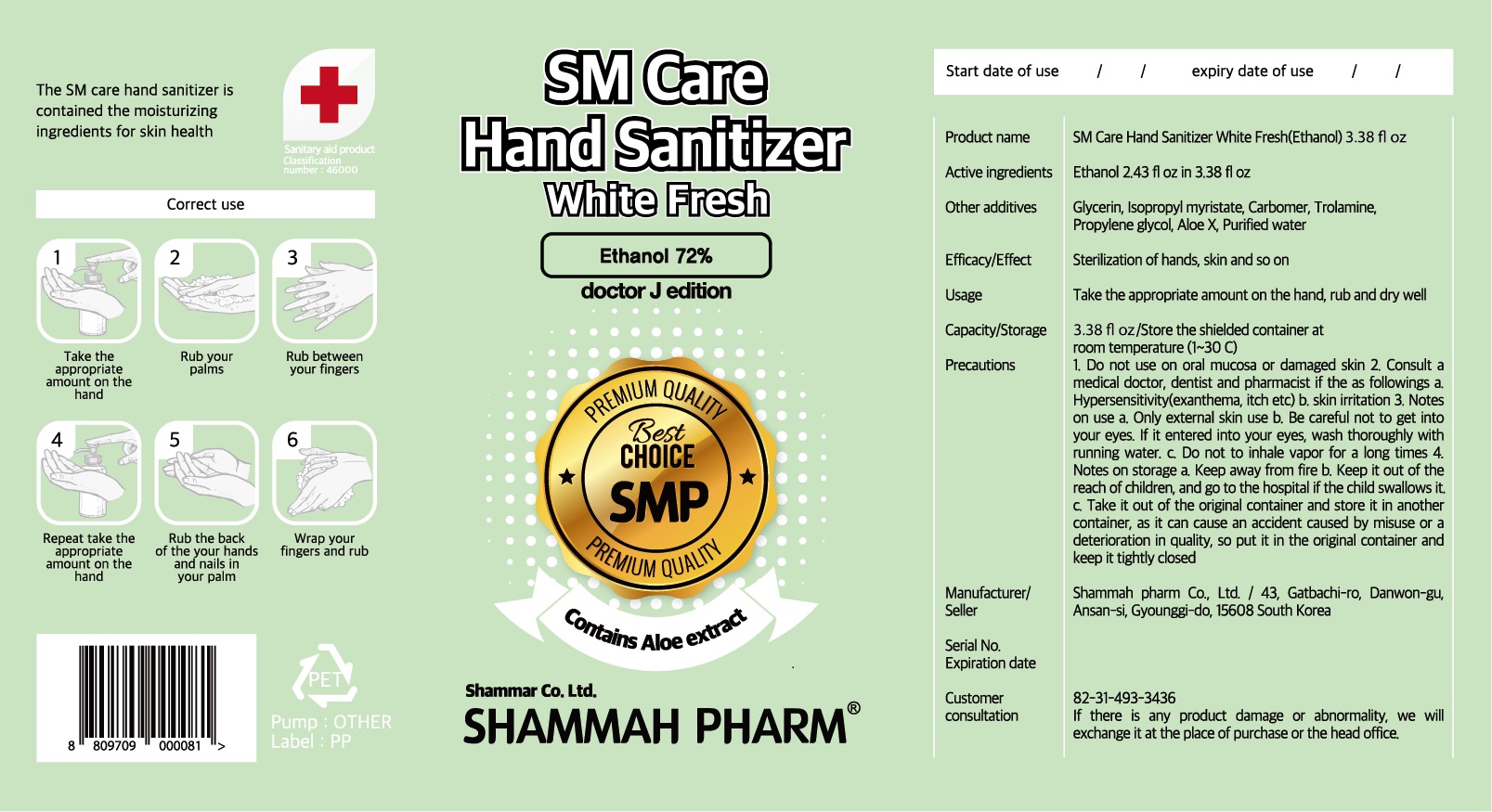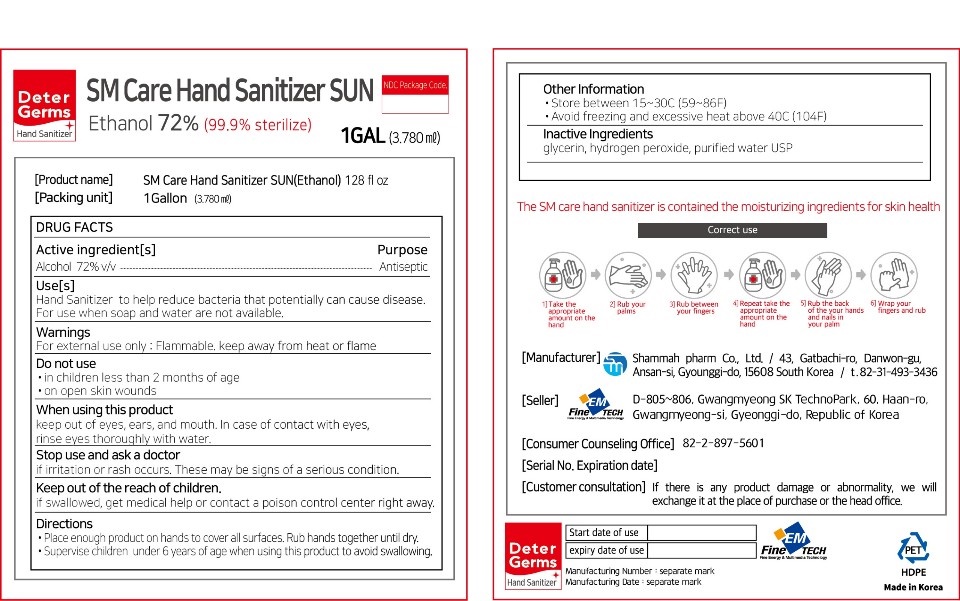 DRUG LABEL: SM Care Hand Sanitizer sun 72%
NDC: 75697-0002 | Form: GEL
Manufacturer: shammah pharm
Category: otc | Type: HUMAN OTC DRUG LABEL
Date: 20200908

ACTIVE INGREDIENTS: ALCOHOL 72 mL/100 mL
INACTIVE INGREDIENTS: TROLAMINE; WATER; ALOE VERA LEAF; CARBOMER 940

Drug Facts

ACTIVE INGREDIENT

ethanol

PURPOSE

sterilization of hands, skin and so on

KEEP OUT OF REACH OF THE CHILDREN

INDICATIONS AND USAGE

take appropriate amount on the hand, rub and dry well

WARNINGS

■ Flammable. Keep away from fire or flame.

■ For external use only.

■ Do not use in eyes.

■ lf swallowed, get medical help promptly.

■ Stop use, ask doctor lf irritation occurs.

■ Keep out of reach of children.

DOSAGE AND ADMINISTRATION

for external use only

INACTIVE INGREDIENT

glycerin, isopropyl myristate, carbomer, trolamine, propylene glycol, acoe x, water